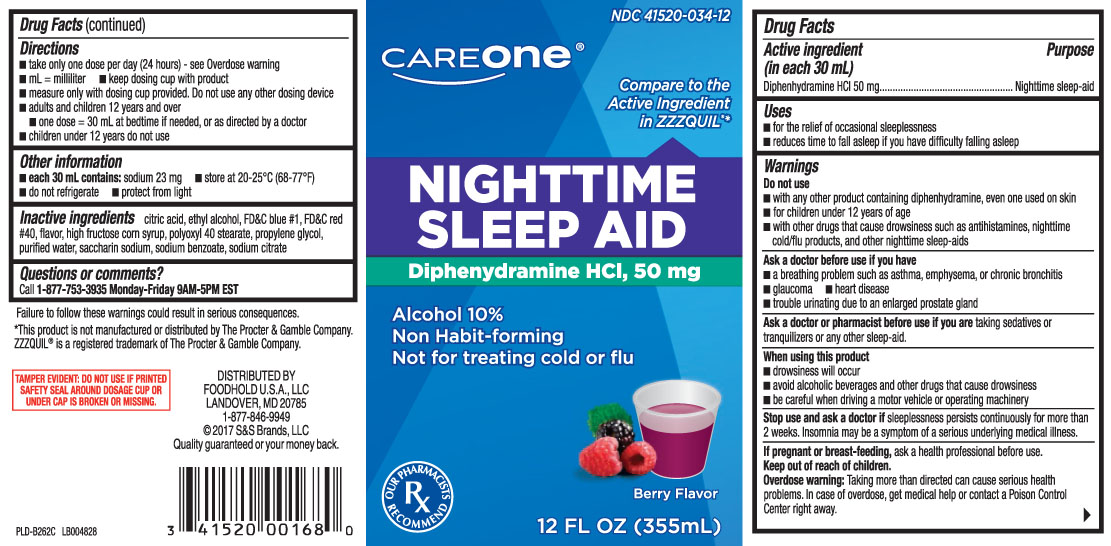 DRUG LABEL: Nighttime Sleep Aid
NDC: 41520-034 | Form: LIQUID
Manufacturer: Care One (American Sales Company)
Category: otc | Type: HUMAN OTC DRUG LABEL
Date: 20240304

ACTIVE INGREDIENTS: DIPHENHYDRAMINE HYDROCHLORIDE 50 mg/30 mL
INACTIVE INGREDIENTS: ANHYDROUS CITRIC ACID; PROPYLENE GLYCOL; POLYOXYL 40 STEARATE; WATER; SODIUM BENZOATE; SACCHARIN SODIUM ANHYDROUS; TRISODIUM CITRATE DIHYDRATE; HIGH FRUCTOSE CORN SYRUP; FD&C BLUE NO. 1; ALCOHOL; FD&C RED NO. 40

Drug Facts

Active ingredient (in each 30 mL)

Diphenhydramine HCl 50 mg

Purpose

Nighttime sleep-aid

Uses

- for the relief of occasional sleeplessness
- reduces time to fall asleep if you have difficulty falling asleep

Warnings

Do not use

- with any other product containing diphenhydramine, even one used on the skin
- for children under 12 years of age
- with other drugs that cause drowsiness such as antihistamines, nighttime cold/flu products, and other nighttime sleep-aids

Ask a doctor before use if you have

- heart disease
- glaucoma
- breathing problem such as asthma,emphysema, or chronic bronchitis
- trouble urinating due to an enlarged prostate gland

Ask a doctor or pharmacist before use if you are

taking sedatives or tranquilizers or any other sleep-aid.

When using this product

- drowsiness will occur
- avoid alcoholic drinks and other drugs that cause drowsiness
- be careful when driving a motor vehicle or operating machinery

Stop use and ask a doctor if

sleeplessness persists continuously for more than 2 weeks. Insomnia may be a symptom of serious underlying medical illness.

If pregnant or breast-feeding,

ask a health professional before use.

Keep out of reach of children.

Overdose warning: Taking more than directed can cause serious health problems. in case of overdose, get medical help or contact a Poison Control Center right away.

Directions

- take only one dose per day (24 hours) - (see overdose warning)
- mL=milliliter
- measure only with dosing cup provided.Do not use any other dosing device
- keep dosing cup with product
- adults and children 12 years and over
  - one dose=30 mL at bedtime if needed, or as directed by a doctor
- children under 12 years do not use

Other information

- each 30 mL contains: sodium 23 mg
- store at 20-25ºC (68-77ºF)
- do not refrigerate
- protect from light

Inactive ingredients

citric acid, ethyl alcohol, FD&C blue #1, FD&C red #40, flavor, high fructose corn syrup, polyoxyl 40 stearate, propylene glycol, purified water, saccharin sodium , sodium benzoate, trisodium citrate dihydrate

Questions or comments?

Call 1-877-753-3935 Monday-friday 9AM-5PM EST

Principal Display Panel

Compare to the Active Ingredient in ZZZQUIL®*

NIGHTTIME SLEEP AID

Diphenhydramine HCI 50 mg

Alcohol 10%

Non-Habit-Forming

Not for treating cold or flu

Berry Flavor

FL OZ (mL)

Failure to follow these warnings could result in serious consequences

TAMPER EVIDENT: DO NOT USE IF PRINTED SAFETY SEAL AROUND DOSAGE CUP OR UNDER CAP IS BROKEN OR MISSING.

*This product is not manufactured or distributed by The Procter & Gamble Company. ZZZQUIL® is a registered trademark of The Procter & Gamble Company.

DISTRIBUTED BY

FOODHOLD USA LLC

LANDOVER, MD 20785

1-877-846-9949

Package Label

CAREONE Nighttime Sleep Aid